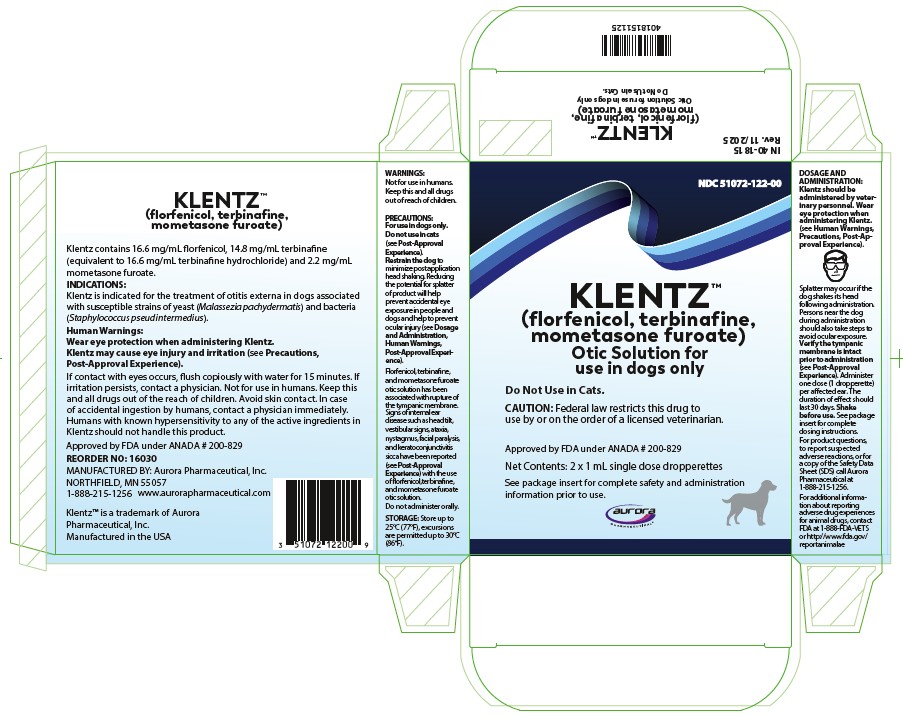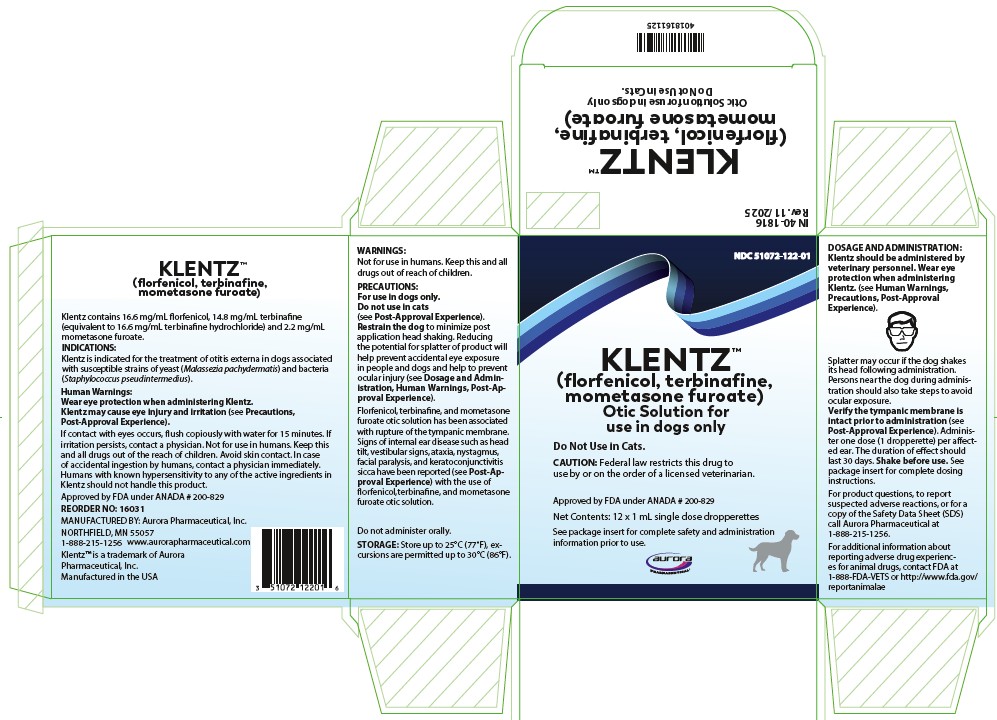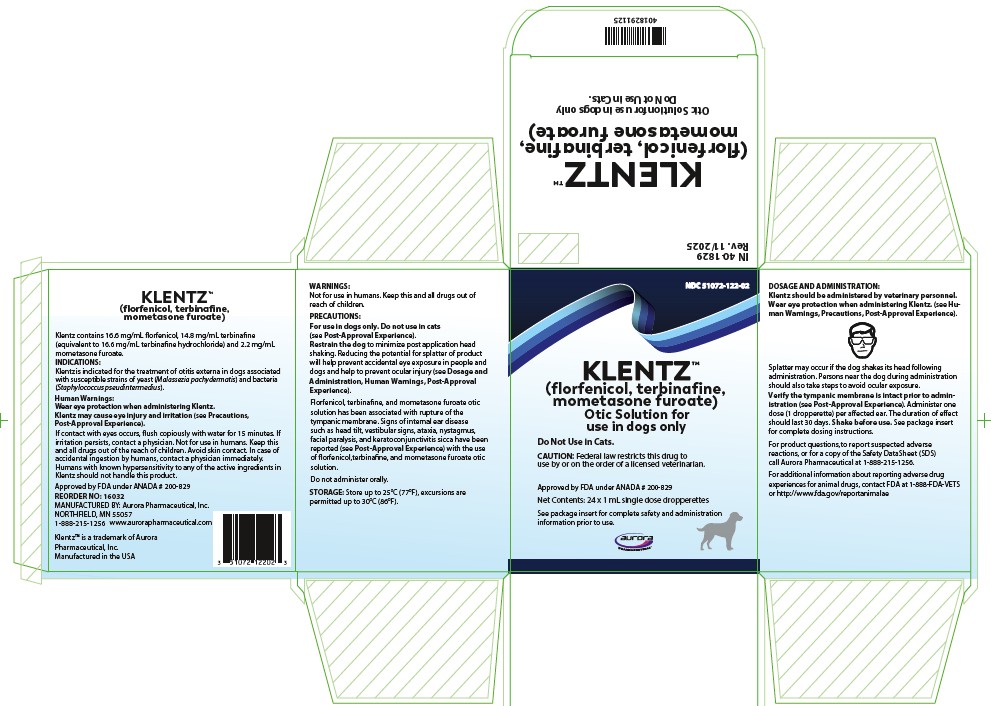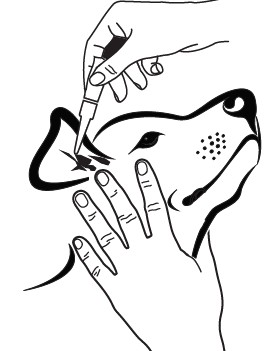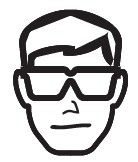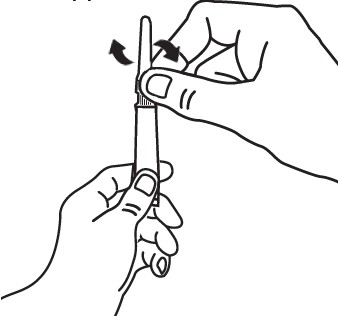 DRUG LABEL: Klentz
NDC: 51072-122 | Form: SOLUTION
Manufacturer: Aurora Pharmaceutical, Inc
Category: animal | Type: PRESCRIPTION ANIMAL DRUG LABEL
Date: 20260113

ACTIVE INGREDIENTS: FLORFENICOL 16.6 mg/1 mL; TERBINAFINE 14.8 mg/1 mL; MOMETASONE FUROATE 2.2 mg/1 mL

Klentz™
(florfenicol, terbinafine, mometasone furoate)

Otic Solution for use in dogs only

Do Not Use in Cats.

Antibacterial, antifungal, and anti-inflammatory

CAUTION: Federal law restricts this drug to use by or on the order of a licensed veterinarian.

DESCRIPTION:

Klentz contains 16.6 mg/mL florfenicol, 14.8 mg/mL terbinafine (equivalent to 16.6 mg/mL terbinafine hydrochloride) and 2.2 mg/mL mometasone furoate. Inactive ingredients include purified water, propylene carbonate, propylene glycol, ethyl alcohol, and polyethylene glycol.

INDICATIONS:

Klentz is indicated for the treatment of otitis externa in dogs associated with susceptible strains of yeast (Malassezia pachydermatis) and bacteria (Staphylococcus pseudintermedius).

DOSAGE AND ADMINISTRATION:

Klentz should be administered by veterinary personnel.

Wear eye protection when administering Klentz. (see Human Warnings, Precautions, Post-Approval Experience).

Splatter may occur if the dog shakes its head following administration. Persons near the dog during administration should also take steps to avoid ocular exposure.

Shake before use.

Verify the tympanic membrane is intact prior to administration. (see Contraindications, Precautions, Post-Approval Experience).

Administer one dose (1 dropperette) per affected ear.

1. Clean and dry the external ear canal before administering the product.

2. Verify the tympanic membrane is intact prior to administration.

3. Remove single dose dropperette from the package.

4. While holding the dropperette in an upright position, twist the cap to open the dropperette. The cap does not come off the dropperette.

5. Insert the tapered tip of the dropperette into the affected external ear canal and squeeze to instill the entire contents (1 mL) into the affected ear.

6. Gently massage the base of the ear to allow distribution of the solution.

Restrain the dog to minimize post application head shaking to reduce potential for splatter of product and accidental eye exposure in people and dogs (see Post-Approval Experience).

7. Repeat with other ear as prescribed.

8. The duration of the effect should last 30 days. Cleaning the ear after dosing may affect product effectiveness.

CONTRAINDICATIONS:

Do not use in dogs with known tympanic membrane perforation (see Precautions).

Klentz is contraindicated in dogs with known or suspected hypersensitivity to florfenicol, terbinafine hydrochloride, or mometasone furoate.

WARNINGS:

Human Warnings: Klentz may cause eye injury and irritation (see Precautions, Post-Approval Experience).

If contact with eyes occurs, flush copiously with water for at least 15 minutes. If irritation persists, contact a physician.

Humans with known hypersensitivity to any of the active ingredients in Klentz should not handle this product.

Not for use in humans. Keep this and all drugs out of the reach of children. Avoid skin contact. In case of accidental ingestion by humans, contact a physician immediately.

PRECAUTIONS:

For use in dogs only. Do not use in cats (see Post-Approval Experience).

Wear eye protection when administering Klentz and restrain the dog to minimize post application head shaking. Reducing the potential for splatter of product will help prevent accidental eye exposure in people and dogs and help to prevent ocular injury (see Dosage and Administration, Human Warnings, Post-Approval Experience).

Proper patient selection is important when considering the benefits and risks of using Klentz. The integrity of the tympanic membrane should be confirmed before administering the product.

Florfenicol, terbinafine, and mometaone furoate otic solution has been associated with rupture of the tympanic membrane. Reevaluate the dog if hearing loss or signs of vestibular dysfunction are observed during treatment.

Signs of internal ear disease such as head tilt, vestibular signs, ataxia, nystagmus, facial paralysis, and keratoconjunctivitis sicca have been reported (see Post-Approval Experience) with the use of florfenicol, terbinafine, and mometasone furoate otic solution.

Do not administer orally.

Use of topical otic corticosteroids has been associated with adrenocortical suppression and iatrogenic hyperadrenocorticism in dogs (see Animal Safety).

Use with caution in dogs with impaired hepatic function (see Animal Safety).

The safe use of Klentz in dogs used for breeding purposes, during pregnancy, or in lactating bitches, has not been evaluated.

ADVERSE REACTIONS:

In a field study conducted in the United States (see Effectiveness), there were no directly attributable adverse reactions in 146 dogs administered florfenicol, terbinafine, and mometasone furoate otic solution.

POST-APPROVAL EXPERIENCE (2019):

The following adverse events are based on post-approval adverse drug experience reporting for florfenicol, terbinafine, and mometasone furoate otic solution. Not all adverse events are reported to FDA/CVM. It is not always possible to reliably estimate the adverse event frequency or establish a causal relationship to product exposure using these data.

In humans, accidental exposure leading to corneal ulcers and other ocular injuries such as eye irritation and redness have been reported. Exposure occurred when the dog shook its head after application of florfenicol, terbinafine, and mometasone furoate otic solution. Skin irritation has also been reported.

In dogs, the adverse events reported are presented below in decreasing order of reporting frequency:
Ear discharge, head shaking, ataxia, internal ear disorder (head tilt and vestibular), deafness, emesis, nystagmus, pinnal irritation and ear pain, keratoconjunctivitis sicca, vocalization, corneal ulcer, cranial nerve disorder (facial paralysis), tympanic membrane rupture.

Klentz (florfenicol, terbinafine, and mometasone furoate) otic solution is not approved for use in cats. The adverse events reported following extra-label use in cats are presented below in decreasing order of reporting frequency:
Ataxia, anorexia, internal ear disorder (head tilt and vestibular), Horner’s syndrome (third eyelid prolapse and miosis), nystagmus, lethargy, anisocoria, head shake, emesis, tympanic rupture, and deafness.

CONTACT INFORMATION:

To report suspected adverse drug experiences, for technical assistance, or to obtain a copy of the Safety Data Sheet (SDS), contact Aurora Pharmaceutical at 1-888-215-1256.

For additional information about reporting adverse drug experiences for animal drugs, contact FDA at 1-888-FDA-VETS or http://www.fda.gov/reportanimalae

Information for Dog Owners:

Owners should be aware that adverse reactions may occur following administration of Klentz and should be instructed to observe the dog for signs such as ear pain and irritation, vomiting, head shaking, head tilt, incoordination, eye pain and ocular discharge (see Post-Approval Experience). Owners should be advised to contact their veterinarian if any of the above signs are observed.

Owners should also be informed that splatter may occur if the dog shakes its head following administration of Klentz which may lead to ocular exposure. Eye injuries, including corneal ulcers, have been reported in humans and dogs associated with head shaking and splatter following administration. Owners should be careful to avoid ocular exposure (see Precautions, Post-Approval Experience).

PHARMACOLOGY:

Klentz otic solution is a fixed combination of three active substances: florfenicol (antibacterial), terbinafine (antifungal), and mometasone furoate (steroidal anti-inflammatory). Florfenicol is a bacteriostatic antibiotic which acts by inhibiting protein synthesis. Terbinafine is an antifungal which selectively inhibits the early synthesis of ergosterol. Mometasone furoate is a glucocorticosteroid with anti-inflammatory activity.

MICROBIOLOGY:

The compatibility and additive effect of each of the components in CLARO solution was demonstrated in a component effectiveness and non-interference study. An in vitro study of organisms collected from clinical cases of otitis externa in dogs enrolled in the clinical effectiveness study determined that florfenicol and terbinafine hydrochloride inhibit the growth of bacteria and yeast commonly associated with otitis externa in dogs. No consistent synergistic or antagonistic effect of the two antimicrobials was demonstrated. The addition of mometasone furoate to the combination did not impair antimicrobial activity to any clinically significant extent. In a field study (see Effectiveness), at least 10 isolates from successfully treated cases were obtained for S. pseudintermedius and M. pachydermatis.

EFFECTIVENESS:

In a well-controlled, double-masked field study, florfenicol, terbinafine, and mometasone furoate otic solution was evaluated against a vehicle control in 221 dogs with otitis externa. One hundred and forty six dogs were treated with florfenicol, terbinafine, and mometasone furoate otic solution and 75 dogs were treated with the vehicle control. All dogs were evaluated for safety. Treatment (1 mL) was administered once on Day 0 to the affected ear(s). Prior to treatment, the ear(s) was cleaned with saline. The dogs were evaluated on Days 0, 7, 14, and 30. Blood work and urinalysis were obtained on Day 0 pre-treatment and Day 30 at study completion. Four clinical signs associated with otitis externa were evaluated: erythema, exudate, swelling, and ulceration. Success was based on clinical improvement at Day 30. Of the 183 dogs included in the effectiveness evaluation, 72.5% of dogs administered florfenicol, terbinafine, and mometasone furoate otic solution were successfully treated, compared to 11.1% of the dogs in the vehicle-control group (p = 0.0001).

ANIMAL SAFETY:

In a target animal safety study, florfenicol, terbinafine, and mometasone furoate otic solution was administered aurally to 12-week-old Beagle puppies (4 dogs/sex/group) at 0X, 1X, 3X, and 5X the recommended dose once every 2 weeks for a total dosing period of 28 days (3 times the treatment duration). No clinically relevant treatment-related findings were noted in hearing tests, body weight, weight gain, or food consumption. Florfenicol, terbinafine, and mometasone furoate otic solution administration was associated with post-treatment ear wetness or clear aural exudate, increased absolute neutrophil count, decreased absolute lymphocyte and eosinophil counts, suppression of the adrenal cortical response to ACTH-stimulation, decreased adrenal weight and atrophy of the adrenal cortex, increased liver weight with hepatocellular enlargement/cytoplasmic change, and decreased thymus weight. Other potentially treatment-related effects included mild changes to AST, total protein, inorganic phosphorus, creatinine, and calcium.

STORAGE INFORMATION:

Store up to 25°C (77°F), excursions are permitted up to 30°C (86°F).

HOW SUPPLIED:

Klentz solution is supplied in a single-use dropperette in a blister.
Each dropperette contains one 1 mL dose.
Klentz is available in cartons of two, twelve, or twenty-four dropperettes.

Manufactured by:
Aurora Pharmaceutical, Inc.
Northfield, MN 55057
1-888-215-1256 www.aurorapharmaceutical.com

Approved by FDA under ANADA # 200-829

Principal Display Panel - 1 mL Carton Label

KLENTZ™
(florfenicol, terbinafine,
mometasone furoate)

Otic Solution for use in dogs only

Do Not Use in Cats.

CAUTION: Federal law restricts this drug to use by or on the order of a licensed veterinarian.

Approved by FDA under ANADA # 200-829

Net Contents: 2 x 1 mL single dose dropperettes

See package insert for complete safety and administration information prior to use.

IN 40-1815 Rev. 11/2025

KLENTZ™

(florfenicol, terbinafine,
mometasone furoate)

Otic Solution for use in dogs only

Do Not Use in Cats.

CAUTION: Federal law restricts this drug to use by or on the order of a licensed veterinarian.

Approved by FDA under ANADA # 200-829

Net Contents: 12 x 1 mL single dose dropperettes

IN 40-1816 Rev. 11/2025

KLENTZ™
(florfenicol, terbinafine,
mometasone furoate)

Otic Solution for use in dogs only

Do Not Use in Cats.

CAUTION: Federal law restricts this drug to use by or on the order of a licensed veterinarian.

Approved by FDA under ANADA # 200-829

Net Contents: 24 x 1 mL single dose dropperettes

IN 40-1829 Rev. 11/2025